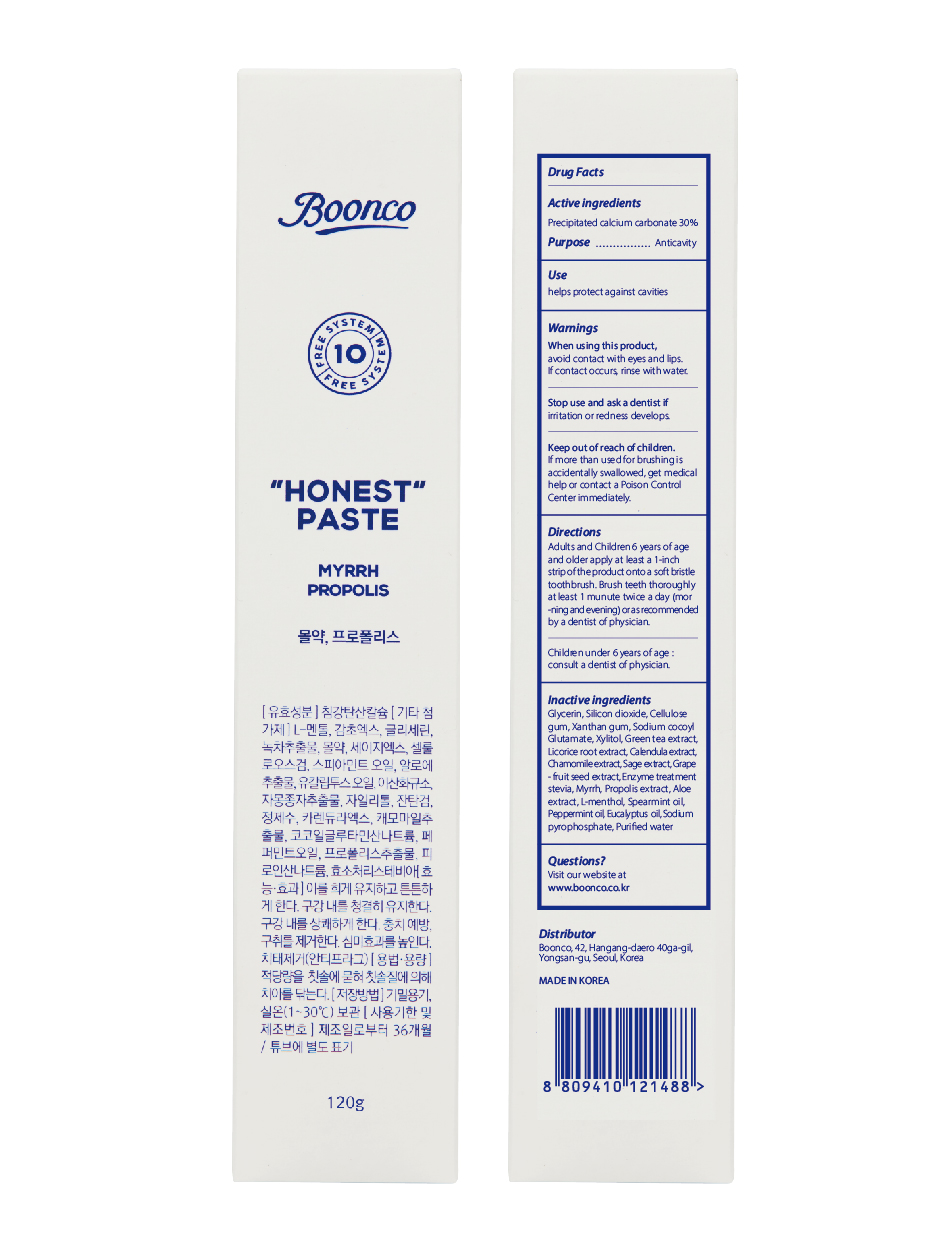 DRUG LABEL: Honest-Paste
NDC: 80925-202 | Form: PASTE
Manufacturer: BOONCO Co., Ltd
Category: otc | Type: HUMAN OTC DRUG LABEL
Date: 20220111

ACTIVE INGREDIENTS: CALCIUM CARBONATE 30 g/100 g
INACTIVE INGREDIENTS: SODIUM COCOYL GLUTAMATE; GLYCYRRHIZA GLABRA; MYRRH; SAGE; ALOE VERA LEAF; XYLITOL; GREEN TEA LEAF; GLYCERIN; SILICON DIOXIDE; XANTHAN GUM; PEPPERMINT OIL; CARBOXYMETHYLCELLULOSE SODIUM; LEVOMENTHOL; SPEARMINT OIL; CALENDULA OFFICINALIS FLOWER; CITRUS MAXIMA SEED; PROPOLIS WAX; CHAMOMILE; SODIUM PYROPHOSPHATE; EUCALYPTUS OIL; WATER

80925-202

Active ingredients

Precipitated calcium carbonate 30%

Purpose

Anticavity

Use

helps protect against cavities

Warnings

When using this product, avoid contact with eyes and lips. If contact occurs, rinse with water.

Stop use and ask a dentist if

irritation or redness develops.

Keep out of reach of children.

If more than used for brushing is accidentally swallowed, get medical help or contact a Poison Control Center immediately.

Directions

- adults and children 6 years of age and older apply at least a 1-inch strip of the product onto a soft bristle toothbrush. Brush teeth thoroughly at least 1 minute twice a day (morning and evening) or as recommended by a dentist or physician.
- children under 6 years of age: consult a dentist or physician

Inactive ingredients

glycerin, silicon dioxide, cellulose gum, xanthan gum, sodium cocoyl glutamate, xylitol, green tea extract, licorice root extract, calendula extract, chamomile extract, sage extract, grapefruit seed extract, enzyme treatment stevia, myrrh, propolis extract, aloe extract, l-menthol, spearmint oil, peppermint oil, eucalyptus oil, sodium pyrophosphate, purified water